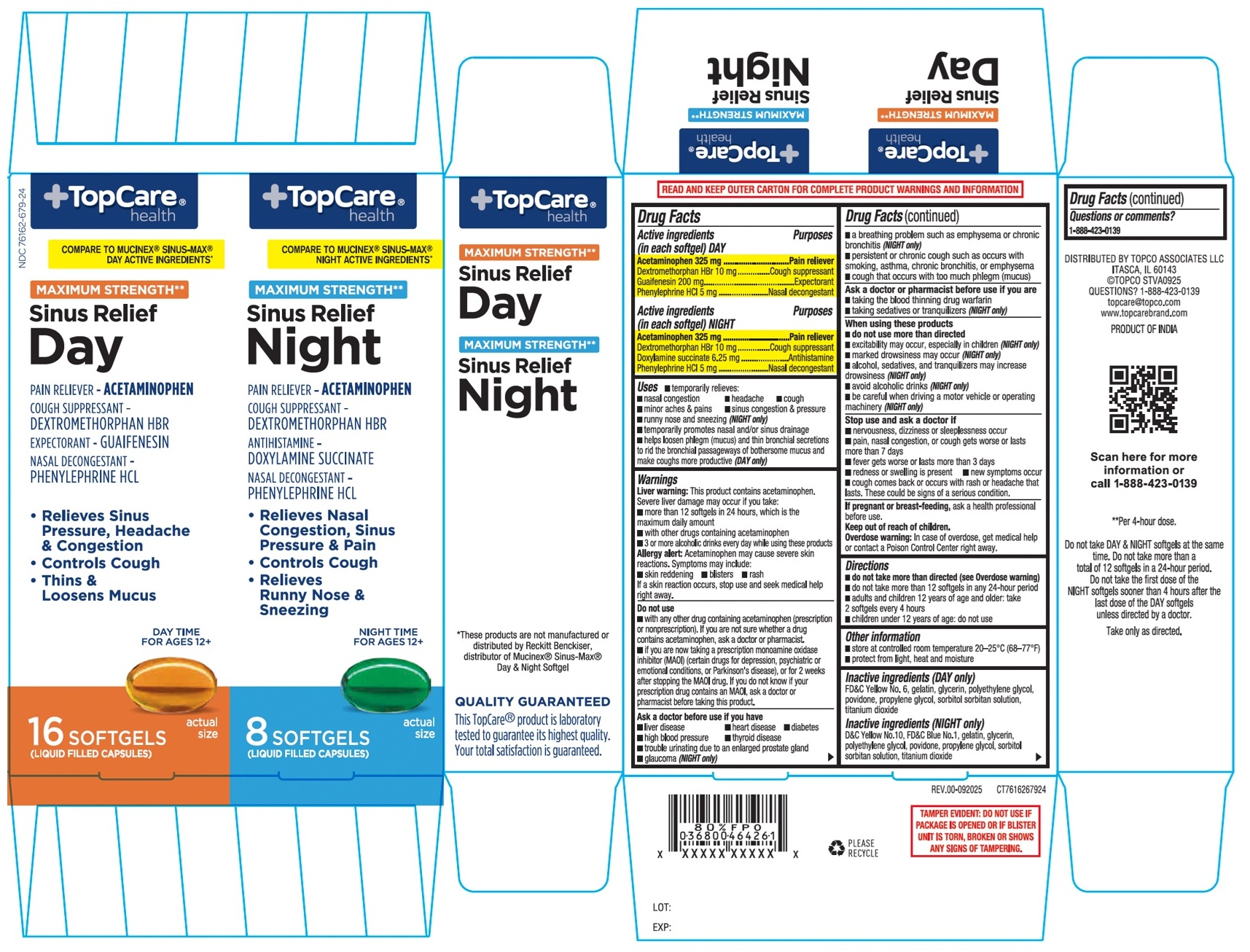 DRUG LABEL: MAXIMUM STRENGTH Sinus Relief Day and Night SOFTGELS - 24 ct
NDC: 76162-679 | Form: KIT | Route: ORAL
Manufacturer: Topco Associates LLC
Category: otc | Type: HUMAN OTC DRUG LABEL
Date: 20251210

ACTIVE INGREDIENTS: ACETAMINOPHEN 325 mg/1 1; DEXTROMETHORPHAN HYDROBROMIDE 10 mg/1 1; GUAIFENESIN 200 mg/1 1; PHENYLEPHRINE HYDROCHLORIDE 5 mg/1 1; ACETAMINOPHEN 325 mg/1 1; DEXTROMETHORPHAN HYDROBROMIDE 10 mg/1 1; DOXYLAMINE SUCCINATE 6.25 mg/1 1; PHENYLEPHRINE HYDROCHLORIDE 5 mg/1 1
INACTIVE INGREDIENTS: FD&C YELLOW NO. 6; GELATIN, UNSPECIFIED; GLYCERIN; POLYETHYLENE GLYCOL, UNSPECIFIED; POVIDONE, UNSPECIFIED; PROPYLENE GLYCOL; SORBITOL; SORBITAN; TITANIUM DIOXIDE; D&C YELLOW NO. 10; FD&C BLUE NO. 1; GELATIN, UNSPECIFIED; GLYCERIN; POLYETHYLENE GLYCOL, UNSPECIFIED; POVIDONE, UNSPECIFIED; PROPYLENE GLYCOL; SORBITOL; SORBITAN; TITANIUM DIOXIDE

MAXIMUM STRENGTH** Sinus Relief Day and Night SOFTGELS

Active ingredients (in each softgel) DAY

Acetaminophen 325 mg
Dextromethorphan HBr 10 mg
Guaifenesin 200 mg
Phenylephrine HCl 5 mg

Active ingredients (in each softgel) NIGHT

Acetaminophen 325 mg
Dextromethorphan HBr 10 mg
Doxylamine succinate 6.25 mg
Phenylephrine HCl 5 mg

Purposes

Pain reliever
Cough suppressant
Expectorant
Nasal decongestant

Purposes

Pain reliever
Cough suppressant
Antihistamine
Nasal decongestant

Uses

• temporarily relieves:
• nasal congestion • headache • cough
• minor aches & pains • sinus congestion & pressure
• runny nose and sneezing (NIGHT only)
• temporarily promotes nasal and/or sinus drainage
• helps loosen phlegm (mucus) and thin bronchial secretions to rid the bronchial passageways of bothersome mucus and make coughs more productive (DAY only)

Warnings

Liver warning: This product contains acetaminophen. Severe liver damage may occur if you take:
• more than 12 softgels in 24 hours, which is the maximum daily amount
• with other drugs containing acetaminophen
• 3 or more alcoholic drinks every day while using these products
Allergy alert: Acetaminophen may cause severe skin reactions. Symptoms may include:
• skin reddening • blisters • rash
If a skin reaction occurs, stop use and seek medical help right away.

Do not use
• with any other drug containing acetaminophen (prescription or nonprescription). If you are not sure whether a drug contains acetaminophen, ask a doctor or pharmacist.
• if you are now taking a prescription monoamine oxidase inhibitor (MAOI) (certain drugs for depression, psychiatric or emotional conditions, or Parkinson's disease), or for 2 weeks after stopping the MAOI drug. If you do not know if your prescription drug contains an MAOI, ask a doctor or pharmacist before taking this product.

Ask a doctor before use if you have
• liver disease • heart disease • diabetes
• high blood pressure • thyroid disease
• trouble urinating due to an enlarged prostate gland
• glaucoma (NIGHT only)
• a breathing problem such as emphysema or chronic bronchitis (NIGHT only)
• persistent or chronic cough such as occurs with smoking, asthma, chronic bronchitis, or emphysema
• cough that occurs with too much phlegm (mucus)

Ask a doctor or pharmacist before use if you are
• taking the blood thinning drug warfarin
• taking sedatives or tranquilizers (NIGHT only)

When using these products
• do not use more than directed
• excitability may occur, especially in children (NIGHT only)
• marked drowsiness may occur (NIGHT only)
• alcohol, sedatives, and tranquilizers may increase drowsiness (NIGHT only)
• avoid alcoholic drinks (NIGHT only)
• be careful when driving a motor vehicle or operating machinery (NIGHT only)

Stop use and ask a doctor if
• nervousness, dizziness or sleeplessness occur
• pain, nasal congestion, or cough gets worse or lasts more than 7 days
• fever gets worse or lasts more than 3 days
• redness or swelling is present • new symptoms occur
• cough comes back or occurs with rash or headache that lasts. These could be signs of a serious condition.

If pregnant or breast-feeding, ask a health professional before use.

Keep out of reach of children.
Overdose warning: In case of overdose, get medical help or contact a Poison Control Center right away.

Directions

• do not take more than directed (see Overdose warning)
• do not take more than 12 softgels in any 24-hour period
• adults and children 12 years of age and older: take 2 softgels every 4 hours
• children under 12 years of age: do not use

Other information

• store at controlled room temperature between 20-25°C (68-77°F)
• protect from light, heat and moisture

Inactive ingredients (DAY only)

FD&C Yellow No. 6, gelatin, glycerin, polyethylene glycol, povidone, propylene glycol, sorbitol sorbitan solution, titanium dioxide

Inactive ingredients (NIGHT only)

D&C Yellow No.10, FD&C Blue No.1, gelatin, glycerin, polyethylene glycol, povidone, propylene glycol, sorbitol sorbitan solution, titanium dioxide

Questions or comments?

1-888-423-0139

TopCare® health

COMPARE TO MUCINEX® SINUS-MAX® DAY ACTIVE INGREDIENTS*

COMPARE TO MUCINEX® SINUS-MAX® NIGHT ACTIVE INGREDIENTS*

MAXIMUM STRENGTH**

*These products are not manufactured or distributed by Reckitt Benckiser, distributor of Mucinex® Sinus-Max® Day & Night Softgel

QUALITY GUARANTEED

This TopCare® product is laboratory tested to guarantee its highest quality. Your total satisfaction is guaranteed.

READ AND KEEP OUTER CARTON FOR COMPLETE PRODUCT WARNINGS AND INFORMATION

DISTRIBUTED BY TOPCO ASSOCIATES LLC
ITASCA, IL 60143
©TOPCO STVA0925
topcare@topco.com
www.topcarebrand.com

PRODUCT OF INDIA

**Per 4-hour dose.

Do not take DAY & NIGHT softgels at the same time. Do not take more than a total of 12 softgels in a 24-hour period. Do not take the first dose of the NIGHT softgels sooner than 4 hours after the last dose of the DAY softgels unless directed by a doctor.

Take only as directed.

TAMPER EVIDENT: DO NOT USE IF PACKAGE IS OPENED OR IF BLISTER UNIT IS TORN, BROKEN OR SHOWS ANY SIGNS OF TAMPERING.